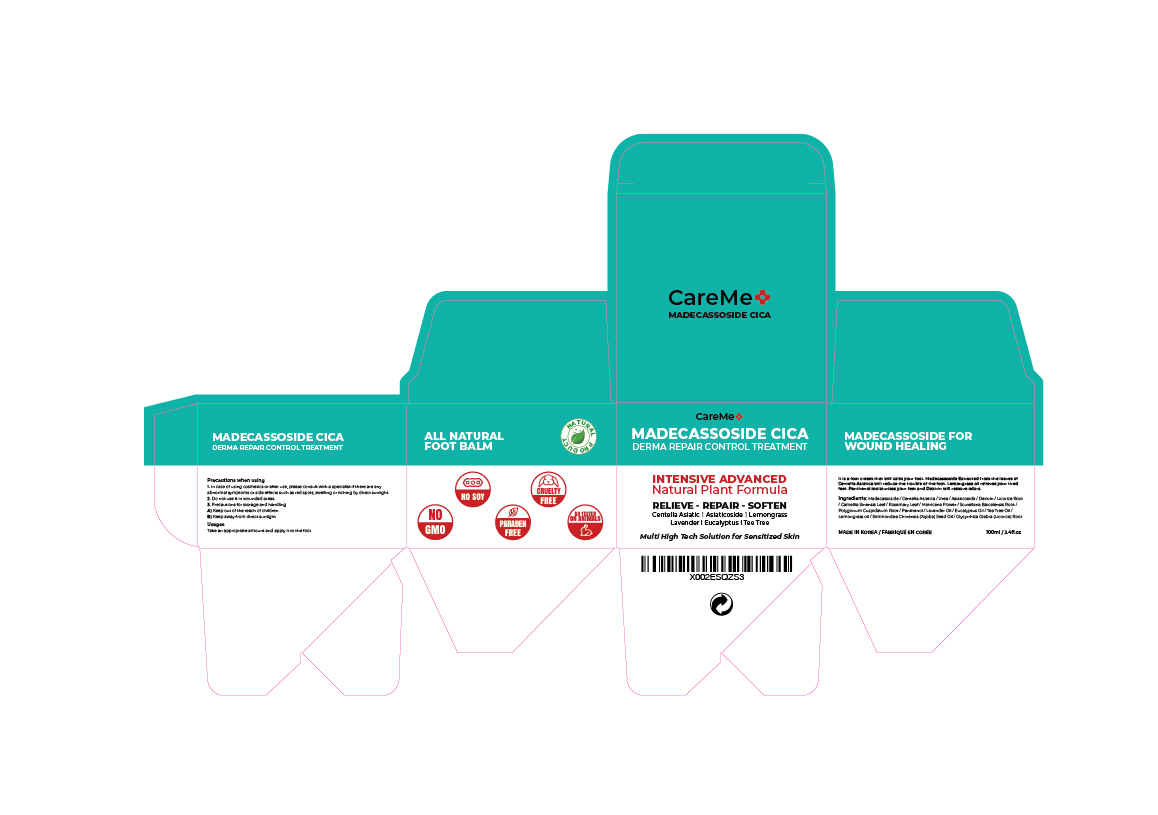 DRUG LABEL: CareMe Madecassoside Cica Derma Repair Control Treatment
NDC: 73771-0001 | Form: CREAM
Manufacturer: MIRINAGLOBAL
Category: otc | Type: HUMAN OTC DRUG LABEL
Date: 20200321

ACTIVE INGREDIENTS: MADECASSOSIDE 0.1 g/100 mL
INACTIVE INGREDIENTS: PANTHENOL; PALMITIC ACID; WATER; GLYCERIN

Drug Facts

ACTIVE INGREDIENT

Madecassoside

INACTIVE INGREDIENT

Water,MineralOil,Glycerin,CetearylAlcohol,Palmiticacid,StearicAcid,Cyclopentasiloxane,Beeswax,Polysorbate60,SorbitanStearate,GlycerylStearate,PEG-100Stearate,Cyclohexasiloxane,Dimethicone,Urea,SimmondsiaChinensis(Jojoba) seedOil,TocopherylAcetate,Madecassoside,Dextrin,Asiaticoside,SodiumHyaluronate,GlycyrrhizaGlabra(Licorice)RootExtract,CamelliaSinensisLeafExtract,RosmarinusOfficinalis(Rosemary)LeafExtract,CentellaAsiaticaExtract,ChamomillaRecutita(Matricaria)FlowerExtract,ScutellariaBaicalensisRootExtract,PolygonumCuspidatumRootExtract,PolyglutamicAcid,Carbomer,Panthenol,LacticAcid,GlycolicAcid,Tromethamine,ButyleneGlycol,CaprylylGlycol,PentyleneGlycol,Hydroxyacetophenone,1,2-Hexanediol,Ethylhexylglycerin,LavandulaAngustifolia(Lavender)Oil,EucalyptusGlobulusLeafOil,Melaleuca Alternifolia (Tea Tree) Leaf Oil, Cymbopogon Citratus Leaf Oil, Linalool, Limonene

PURPOSE

It is a foot cream that will calm your foot. Madecassoside Extracted from the leaves of Centella Asiatica will reduce the trouble of the foot. Lemongrass oil relieves your tired feet. Panthenol moisturizes your feet and Dextrin will remove odors.

KEEP OUT OF REACH OF THE CHILDREN

INDICATIONS AND USAGE

Take an appropriate amount and apply it to the foot

WARNINGS

1. In case of using cosmetics or after use, please consult with a specialist if there are any abnormal symptoms or side effects such as red spots, swelling or itching by direct sunlight.

2. Do not use it in wounded areas.

3. Precautions for storage and handling

A) Keep out of the reach of children

B) Keep away from direct sunlight

DOSAGE AND ADMINISTRATION

for external use only